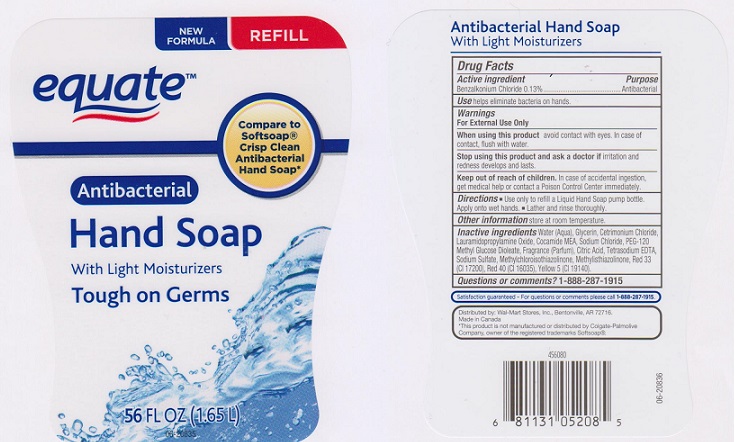 DRUG LABEL: EQUATE
NDC: 49035-721 | Form: LIQUID
Manufacturer: WAL-MART STORES INC
Category: otc | Type: HUMAN OTC DRUG LABEL
Date: 20151127

ACTIVE INGREDIENTS: BENZALKONIUM CHLORIDE 1.3 mg/1 mL
INACTIVE INGREDIENTS: WATER; CETRIMONIUM CHLORIDE; GLYCERIN; LAURAMIDOPROPYLAMINE OXIDE; COCO MONOETHANOLAMIDE; SODIUM CHLORIDE; PEG-120 METHYL GLUCOSE DIOLEATE; CITRIC ACID MONOHYDRATE; EDETATE SODIUM; SODIUM SULFATE; METHYLCHLOROISOTHIAZOLINONE; METHYLISOTHIAZOLINONE; FD&C RED NO. 40; FD&C YELLOW NO. 5; D&C RED NO. 33

DRUG FACTS

Active ingredient

Benzalkonium Chloride 0.13%

Purpose

Antibacterial

Uses

Helps eliminate bacteria on hands.

Warnings

For external use only.

When using this product

avoid contact with eyes. In case of contact, flush with water

Stop using this product and ask a doctor if

irritation and redness develops and lasts

Keep out of reach of children

In case of accidental ingestion, get medical help or contact a Poison Control Center immediately

Directions

- Use only to refill a Liquid Hand Soap pump bottle. Apply onto wet hands
- Lather and rinse thoroughly.

Other information

store at room temperature

Inactive ingredients

Water (Aqua), Glycerin, Cetrimonium Chloride, Lauramidopropylamine Oxide, Cocamide MEA, Sodium Chloride, PEG-120 Methyl Glucose Dioleate, Fragrance (Parfum), Citric Acid, Tetrasodium EDTA, Sodium Sulfate, Methylchloroisothiazolinone, Methylisothiazolinone, Red 33 (CI 17200), Red 40 (CI 16035), Yellow 5 (CI 19140).

Questions or comments?

1-888-287-1915